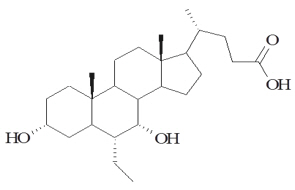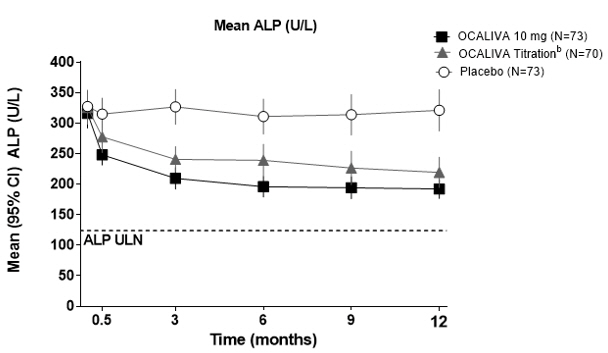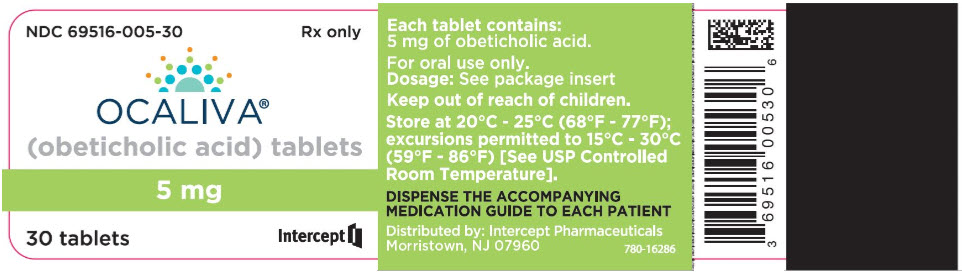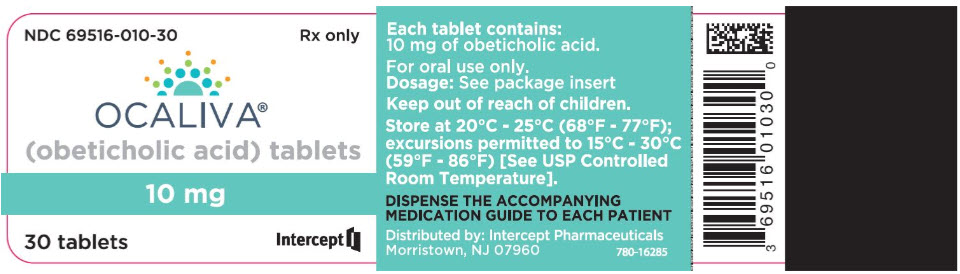 DRUG LABEL: Ocaliva
NDC: 69516-005 | Form: TABLET, FILM COATED
Manufacturer: Intercept Pharmaceuticals Inc
Category: prescription | Type: HUMAN PRESCRIPTION DRUG LABEL
Date: 20241107

ACTIVE INGREDIENTS: OBETICHOLIC ACID 5 mg/1 1
INACTIVE INGREDIENTS: MICROCRYSTALLINE CELLULOSE; SODIUM STARCH GLYCOLATE TYPE A POTATO; MAGNESIUM STEARATE; POLYVINYL ALCOHOL, UNSPECIFIED; TITANIUM DIOXIDE; POLYETHYLENE GLYCOL 3350; TALC; FERRIC OXIDE YELLOW

HIGHLIGHTS OF PRESCRIBING INFORMATION

These highlights do not include all the information needed to use OCALIVA® safely and effectively. See full prescribing information for OCALIVA.
OCALIVA® (obeticholic acid) tablets, for oral use
Initial U.S. Approval: 2016

WARNING: HEPATIC DECOMPENSATION AND FAILURE IN PRIMARY BILIARY CHOLANGITIS PATIENTS WITH CIRRHOSIS

See full prescribing information for complete boxed warning

- Hepatic decompensation and failure, sometimes fatal or resulting in liver transplant, have been reported with OCALIVA treatment in primary biliary cholangitis (PBC) patients with either compensated or decompensated cirrhosis. (5.1)
- OCALIVA is contraindicated in PBC patients with decompensated cirrhosis, a prior decompensation event, or with compensated cirrhosis who have evidence of portal hypertension. (4)
- Permanently discontinue OCALIVA in patients who develop laboratory or clinical evidence of hepatic decompensation, have compensated cirrhosis and develop evidence of portal hypertension, or experience clinically significant hepatic adverse reactions while on treatment. (2.3, 5.1)

1 INDICATIONS AND USAGE

OCALIVA, a farnesoid X receptor (FXR) agonist, is indicated for the treatment of adult patients with primary biliary cholangitis (PBC)

- without cirrhosis or
- with compensated cirrhosis who do not have evidence of portal hypertension,

either in combination with ursodeoxycholic acid (UDCA) with an inadequate response to UDCA or as monotherapy in patients unable to tolerate UDCA.

This indication is approved under accelerated approval based on a reduction in alkaline phosphatase (ALP). An improvement in survival or disease-related symptoms has not been established. Continued approval for this indication may be contingent upon verification and description of clinical benefit in confirmatory trials. (1)

2 DOSAGE AND ADMINISTRATION

Recommended Dosage Regimen

The recommended starting dosage of OCALIVA, for PBC patients without cirrhosis or with compensated cirrhosis who do not have evidence of portal hypertension, who have not achieved an adequate biochemical response to an appropriate dosage of UDCA for at least 1 year or who are intolerant to UDCA follows below:

- Start with a dosage of 5 mg once daily for the first 3 months.
- After the first 3 months, for patients who have not achieved an adequate reduction in ALP and/or total bilirubin and who are tolerating OCALIVA, increase to a maximum dosage of 10 mg once daily. (2.2)

Routinely monitor patients during OCALIVA treatment for biochemical response, tolerability, and progression of PBC. (2.3)

Management of Patients with Intolerable Pruritus

- See full prescribing information for management options. (2.4)

Administration Instructions

- Take with or without food. (2.5)
- For patients taking bile acid binding resins, take OCALIVA at least 4 hours before or 4 hours after taking a bile acid binding resin, or at as great an interval as possible. (7.1)

3 DOSAGE FORMS AND STRENGTHS

Tablets: 5 mg, 10 mg (3)

4 CONTRAINDICATIONS

- decompensated cirrhosis (e.g., Child-Pugh Class B or C) or a prior decompensation event (4)
- compensated cirrhosis with evidence of portal hypertension (e.g., ascites, gastroesophageal varices, persistent thrombocytopenia) (4)
- complete biliary obstruction (4)

5 WARNINGS AND PRECAUTIONS

- Hepatic Decompensation and Failure in PBC Patients with Cirrhosis: Routinely monitor patients for progression of PBC, including hepatic adverse reactions, with laboratory and clinical assessments. Closely monitor patients at risk of hepatic decompensation. Permanently discontinue in patients who develop laboratory or clinical evidence of hepatic decompensation; have compensated cirrhosis and develop evidence of portal hypertension; experience clinically significant hepatic adverse reactions; or develop complete biliary obstruction. Interrupt treatment in patients with severe intercurrent illness. (2.3, 4, 5.1)
- Severe Pruritus: Management strategies include the addition of bile acid binding resins or antihistamines; OCALIVA dosage reduction and/or temporary dosing interruption. (2.4, 5.2)
- Reduction in HDL-C: Monitor for changes in serum lipid levels during treatment. (5.3)

6 ADVERSE REACTIONS

Most common adverse reactions (≥ 5%) are: pruritus, fatigue, abdominal pain and discomfort, rash, oropharyngeal pain, dizziness, constipation, arthralgia, thyroid function abnormality, and eczema. (6.1)

To report SUSPECTED ADVERSE REACTIONS, contact Intercept Pharmaceuticals at 1-844-782-ICPT or FDA at 1-800-FDA-1088 or www.fda.gov/medwatch.

7 DRUG INTERACTIONS

- Warfarin: Potential for decreased INR; monitor INR and adjust the dosage of warfarin, as needed, to maintain the target INR range. (7.2)
- CYP1A2 Substrates with Narrow Therapeutic Index (e.g., theophylline and tizanidine): Potential for increased exposure to CYP1A2 substrates; monitor drug concentrations of CYP1A2 substrates with narrow therapeutic index. (7.3)
- Inhibitors of Bile Salt Efflux Pump (e.g., cyclosporine): Avoid use. If concomitant use is necessary, monitor serum transaminases and bilirubin. (7.4)

FULL PRESCRIBING INFORMATION

WARNING: HEPATIC DECOMPENSATION AND FAILURE IN PRIMARY BILIARY CHOLANGITIS PATIENTS WITH CIRRHOSIS

- Hepatic decompensation and failure, sometimes fatal or resulting in liver transplant, have been reported with OCALIVA treatment in primary biliary cholangitis (PBC) patients with either compensated or decompensated cirrhosis [see Warnings and Precautions (5.1)].
- OCALIVA is contraindicated in PBC patients with decompensated cirrhosis, a prior decompensation event, or with compensated cirrhosis who have evidence of portal hypertension [see Contraindications (4)].
- Permanently discontinue OCALIVA in patients who develop laboratory or clinical evidence of hepatic decompensation; have compensated cirrhosis and develop evidence of portal hypertension; or experience clinically significant hepatic adverse reactions while on treatment [see Dosage and Administration (2.3), Warnings and Precautions (5.1)].

1 INDICATIONS AND USAGE

OCALIVA® is indicated for the treatment of adult patients with primary biliary cholangitis (PBC)

- without cirrhosis or
- with compensated cirrhosis who do not have evidence of portal hypertension,

either in combination with ursodeoxycholic acid (UDCA) with an inadequate response to UDCA or as monotherapy in patients unable to tolerate UDCA.

This indication is approved under accelerated approval based on a reduction in alkaline phosphatase (ALP) [see Clinical Studies (14)]. An improvement in survival or disease-related symptoms has not been established. Continued approval for this indication may be contingent upon verification and description of clinical benefit in confirmatory trials.

2 DOSAGE AND ADMINISTRATION

2.1 Important Dosage and Administration Instructions

Prior to the initiation of OCALIVA, healthcare providers should determine whether the patient has decompensated cirrhosis (e.g., Child-Pugh Class B or C), has had a prior decompensation event, or has compensated cirrhosis with evidence of portal hypertension (e.g., ascites, gastroesophageal varices, persistent thrombocytopenia) because OCALIVA is contraindicated in these patients [see Contraindications (4), Warnings and Precautions (5.1)].

2.2 Recommended Dosage Regimen

The recommended dosage of OCALIVA for PBC patients without cirrhosis or with compensated cirrhosis who do not have evidence of portal hypertension, who have not achieved an adequate biochemical response to an appropriate dosage of UDCA for at least 1 year or are intolerant to UDCA [see Clinical Studies (14)] follows below:

- Start with a dosage of 5 mg once daily for the first 3 months.
- After the first 3 months, for patients who have not achieved an adequate reduction in ALP and/or total bilirubin and who are tolerating OCALIVA, increase to a maximum dosage of 10 mg once daily.

2.3 Monitoring to Assess Safety, Need for OCALIVA Discontinuation

Routinely monitor patients during OCALIVA treatment for biochemical response, tolerability, and progression of PBC. Closely monitor patients with compensated cirrhosis, concomitant hepatic disease (e.g., autoimmune hepatitis, alcoholic liver disease), and/or severe intercurrent illness for new evidence of portal hypertension (e.g., ascites, gastroesophageal varices, persistent thrombocytopenia) or increases above the upper limit of normal in total bilirubin, direct bilirubin, or prothrombin time. Permanently discontinue OCALIVA in patients who develop laboratory or clinical evidence of hepatic decompensation, have compensated cirrhosis and develop evidence of portal hypertension, experience clinically significant hepatic adverse reactions, or develop complete biliary obstruction [see Contraindications (4), Warnings and Precautions (5.1)].

2.4 Management of Patients with Intolerable Pruritus on OCALIVA

For patients with intolerable pruritus on OCALIVA, consider one or more of the following management strategies:

- Add an antihistamine or bile acid binding resin [see Dosage and Administration (2.5), Clinical Studies (14)].
- Reduce the dosage of OCALIVA to:
  - 5 mg every other day, for patients intolerant to 5 mg once daily.
  - 5 mg once daily, for patients intolerant to 10 mg once daily.
- Temporarily interrupt OCALIVA dosing for up to 2 weeks. Restart at a reduced dosage.

For patients whose dosage is reduced or interrupted, titrate the dosage based on biochemical response and tolerability [see Dosage and Administration (2.2)].

Consider discontinuing OCALIVA treatment in patients who continue to experience persistent, intolerable pruritus despite management strategies [see Warnings and Precautions (5.2)].

2.5 Administration Instructions

- Take OCALIVA with or without food.
- For patients taking a bile acid binding resin, take OCALIVA at least 4 hours before or 4 hours after taking the bile acid binding resin, or at as great an interval as possible [see Drug Interactions (7.1), Clinical Studies (14)].

3 DOSAGE FORMS AND STRENGTHS

OCALIVA is available as:

- 5 mg tablet: Off white to yellow, round tablet debossed with "INT" on one side and "5" on the other side.
- 10 mg tablet: Off white to yellow, triangular tablet debossed with "INT" on one side and "10" on the other side.

4 CONTRAINDICATIONS

OCALIVA is contraindicated in patients with:

- decompensated cirrhosis (e.g., Child-Pugh Class B or C) or a prior decompensation event [see Warnings and Precautions (5.1)].
- compensated cirrhosis who have evidence of portal hypertension (e.g., ascites, gastroesophageal varices, persistent thrombocytopenia) [see Warnings and Precautions (5.1)].
- complete biliary obstruction.

5 WARNINGS AND PRECAUTIONS

5.1 Hepatic Decompensation and Failure in PBC Patients with Cirrhosis

Hepatic decompensation and failure, sometimes fatal or resulting in liver transplant, have been reported with OCALIVA treatment in PBC patients with cirrhosis, either compensated or decompensated. Among postmarketing cases reporting it, median time to hepatic decompensation (e.g., new onset ascites) was 4 months for patients with compensated cirrhosis; median time to a new decompensation event (e.g., hepatic encephalopathy) was 2.5 months for patients with decompensated cirrhosis.

Some of these cases occurred in patients with decompensated cirrhosis when they were treated with higher than the recommended dosage for that patient population; however, cases of hepatic decompensation and failure have continued to be reported in patients with decompensated cirrhosis even when they received the recommended dosage.

Hepatotoxicity was observed in the OCALIVA clinical trials. A dose-response relationship was observed for the occurrence of hepatic adverse reactions including jaundice, worsening ascites, and primary biliary cholangitis flare with dosages of OCALIVA of 10 mg once daily to 50 mg once daily (up to 5-times the highest recommended dosage), as early as one month after starting treatment with OCALIVA in two 3-month, placebo-controlled clinical trials in patients with primarily early stage PBC [see Overdosage (10)].

In a pooled analysis of three placebo-controlled clinical trials in patients with primarily early stage PBC, the exposure-adjusted incidence rates for all serious and otherwise clinically significant hepatic adverse reactions, and isolated elevations in liver biochemical tests, per 100 patient exposure years (PEY) were: 5.2 in the OCALIVA 10 mg group (highest recommended dosage), 19.8 in the OCALIVA 25 mg group (2.5-times the highest recommended dosage) and 54.5 in the OCALIVA 50 mg group (5-times the highest recommended dosage) compared to 2.4 in the placebo group.

Patient Management

Routinely monitor patients for progression of PBC, including hepatic adverse reactions, with laboratory and clinical assessments to determine whether drug discontinuation is needed [see Dosage and Administration (2.3)].

Closely monitor patients with compensated cirrhosis, concomitant hepatic disease (e.g., autoimmune hepatitis, alcoholic liver disease), and/or with severe intercurrent illness for new evidence of portal hypertension (e.g., ascites, gastroesophageal varices, persistent thrombocytopenia) or increases above the upper limit of normal in total bilirubin, direct bilirubin, or prothrombin time to determine whether drug discontinuation is needed [see Dosage and Administration (2.3)].

Permanently discontinue OCALIVA in patients who:

- develop laboratory or clinical evidence of hepatic decompensation (e.g., ascites, jaundice, variceal bleeding, hepatic encephalopathy) [see Contraindications (4)].
- have compensated cirrhosis and develop evidence of portal hypertension (e.g., ascites, gastroesophageal varices, persistent thrombocytopenia) [see Contraindications (4)].
- experience clinically significant hepatic adverse reactions.
- develop complete biliary obstruction [see Contraindications (4)].

If severe intercurrent illness occurs, interrupt treatment with OCALIVA and monitor the patient's liver function. After resolution of the intercurrent illness, consider the potential risks and benefits of restarting OCALIVA treatment.

5.2 Severe Pruritus

Severe pruritus was reported in 23% of patients in the OCALIVA 10 mg arm, 19% of patients in the OCALIVA titration arm, and 7% of patients in the placebo arm in Trial 1, a 12-month double-blind randomized controlled clinical trial of 216 patients [see Adverse Reactions (6.1)]. Severe pruritus was defined as intense or widespread itching, interfering with activities of daily living, or causing severe sleep disturbance, or intolerable discomfort, and typically requiring medical interventions. In the subgroup of patients in the OCALIVA titration arm who increased their dosage from 5 mg once daily to 10 mg once daily after 6 months of treatment (n=33), the incidence of severe pruritus was 0% from Months 0 to 6 and 15% from Months 6 to 12. The median time to onset of severe pruritus was 11, 158, and 75 days for patients in the OCALIVA 10 mg, OCALIVA titration, and placebo arms, respectively.

Consider clinical evaluation of patients with new onset or worsening severe pruritus. Management strategies include the addition of bile acid binding resins or antihistamines, OCALIVA dosage reduction, and/or temporary interruption of OCALIVA dosing [see Dosage and Administration (2.4)].

5.3 Reduction in HDL-C

Patients with PBC generally exhibit hyperlipidemia characterized by a significant elevation in total cholesterol primarily due to increased levels of high-density lipoprotein-cholesterol (HDL-C). In Trial 1, dose-dependent reductions from baseline in mean HDL-C levels were observed at 2 weeks in OCALIVA-treated patients, 20% and 9% in the 10 mg and titration arms, respectively, compared to 2% in the placebo arm. At Month 12, the reduction from baseline in mean HDL-C level was 19% in the OCALIVA 10 mg arm, 12% in the OCALIVA titration arm, and 2% in the placebo arm. Nine patients in the OCALIVA 10 mg arm, 6 patients in the OCALIVA titration arm, versus 3 patients in the placebo arm had reductions in HDL-C to less than 40 mg/dL.

Monitor patients for changes in serum lipid levels during treatment. For patients who do not respond to OCALIVA after 1 year at the highest recommended dosage that can be tolerated (maximum of 10 mg once daily), and who experience a reduction in HDL-C, weigh the potential risks against the benefits of continuing treatment.

6 ADVERSE REACTIONS

The following clinically significant adverse reactions are described elsewhere in labeling:

- Hepatic Decompensation and Failure in PBC Patients with Cirrhosis [see Warnings and Precautions (5.1)]
- Severe Pruritus [see Warnings and Precautions (5.2)]
- Reduction in HDL-C [see Warnings and Precautions (5.3)]

6.1 Clinical Trials Experience

Because clinical trials are conducted under widely varying conditions, adverse reaction rates observed in the clinical trials of a drug cannot be directly compared to rates in the clinical trials of another drug and may not reflect the rates observed in practice.

A total of 432 patients with PBC were studied in three double-blind, placebo-controlled clinical trials. Of these patients, 290 were treated with OCALIVA for at least 6 months, 232 were treated for at least 12 months, and 70 were treated for at least 2 years. There were 131 patients who received OCALIVA 10 mg once daily and 70 who received OCALIVA 5 mg once daily.

In Trial 1, 216 patients were randomized (1:1:1) to receive either:

- OCALIVA 10 mg once daily for the entire 12 months of the trial (n=73)
- OCALIVA titration (5 mg once daily for the initial 6 months, with the option to increase to 10 mg once daily for the last 6 months, in patients who were tolerating OCALIVA, but had ALP 1.67-times ULN or greater, and/or total bilirubin greater than ULN, or less than 15% ALP reduction) (n=70); or
- placebo (n=73).

During the trial, OCALIVA or placebo was administered in combination with UDCA in 93% of patients and as monotherapy in 7% of patients who were unable to tolerate UDCA. The overall discontinuation rate was 12% in the OCALIVA 10 mg arm, 10% in the OCALIVA titration arm, and 4% in the placebo arm.

The recommended starting dosage of OCALIVA is 5 mg orally once daily for 3 months with titration to 10 mg once daily based upon tolerability and response [see Dosage and Administration (2.2)]. Initiation of therapy with OCALIVA 10 mg once daily is not recommended due to an increased risk of pruritus.

The most common adverse reactions in Trial 1 occurring in at least 5% of patients in either OCALIVA treatment arm and at an incidence at least 1% higher than the placebo treatment arm are shown in Table 1.

Table 1: Most Common Adverse Reactions in Adult Patients with PBC in Trial 1 by Treatment Arm with or without UDCA [In the trial there were 16 patients (7%) who were intolerant and did not receive concomitant UDCA: 6 patients (8%) in the OCALIVA 10 mg arm, 5 patients (7%) in the OCALIVA titration arm, and 5 patients (7%) in the placebo arm.]
 |  |  | Placebo N=73 %
Adverse Reaction [Occurring in greater than or equal to 5% of patients in either OCALIVA treatment arm and at an incidence greater than or equal to1% higher than in the placebo treatment arm.] | OCALIVA 10 mg N=73 % | OCALIVA Titration [Patients randomized to OCALIVA titration received OCALIVA 5 mg once daily for the initial 6-month period. At Month 6, patients who were tolerating OCALIVA, but had an ALP 1.67-times ULN or greater, and/or total bilirubin greater than ULN, or less than 15% ALP reduction were eligible for titration from 5 mg once daily to 10 mg once daily for the final 6 months of the trial.] N=70 % | Placebo N=73 %
Pruritus [Includes skin eruptions, prurigo, pruritus, pruritus generalized, eye pruritus, ear pruritus, anal pruritus, vulvovaginal pruritus, rash pruritic.] | 70 | 56 | 38
Fatigue [Includes fatigue, tiredness, asthenia.] | 25 | 19 | 15
Abdominal pain and discomfort [Includes abdominal pain upper, abdominal pain, abdominal discomfort, abdominal pain lower, abdominal tenderness, gastrointestinal pain.] | 10 | 19 | 14
Rash [Includes urticaria, rash, rash macular, rash papular, rash maculo-papular, heat rash, urticaria cholinergic.] | 10 | 7 | 8
Arthralgia | 10 | 6 | 4
Oropharyngeal pain | 8 | 7 | 1
Dizziness [Includes dizziness, syncope, presyncope.] | 7 | 7 | 5
Constipation | 7 | 7 | 5
Peripheral Edema | 7 | 3 | 3
Palpitations | 7 | 3 | 1
Pyrexia | 7 | 0 | 1
Thyroid function abnormality [Includes thyroxine free decreased, blood thyroid stimulating hormone increased, hypothyroidism.] | 4 | 6 | 3
Eczema | 3 | 6 | 0

Hepatic Adverse Reactions

In Trial 1, the following serious or otherwise clinically significant hepatic adverse reactions were reported at the recommended dosage of OCALIVA: one patient in the OCALIVA 10 mg treatment arm experienced ascites; one patient in the OCALIVA titration treatment arm experienced two episodes of ascites and four episodes of hepatic encephalopathy; one patient in the placebo treatment arm experienced variceal bleeding.

Pruritus

Approximately 60% of patients had a history of pruritus upon enrollment in Trial 1. Treatment-emergent pruritus, including all the terms described in Table 1, generally started within the first month following the initiation of treatment with OCALIVA.

The incidence of pruritus was higher in patients who started on OCALIVA 10 mg once daily relative to the OCALIVA titration arm, 70% and 56%, respectively. Discontinuation rates due to pruritus were also higher in patients who started on OCALIVA 10 mg once daily relative to the OCALIVA titration arm, 10% and 1%, respectively.

The number of patients with pruritus who required an intervention (e.g., dosage adjustment, treatment interruption, or initiation of bile acid binding resin or antihistamine) was 30 of 51 patients (59%) in the OCALIVA 10 mg arm, 24 of 39 patients (62%) in the OCALIVA titration arm, and 14 of 28 patients (50%) in the placebo arm.

6.2 Postmarketing Experience

The following adverse reactions have been identified during post-approval use of OCALIVA. Because these reactions are reported voluntarily from a population of uncertain size, it is not always possible to reliably estimate their frequency or establish a causal relationship to drug exposure, particularly in PBC patients who have progressive liver disease.

Hepatobiliary Disorders: liver failure, new onset cirrhosis, increased direct and total bilirubin, new or worsening of jaundice [see Warnings and Precautions (5.1)].

7 DRUG INTERACTIONS

7.1 Bile Acid Binding Resins

Bile acid binding resins such as cholestyramine, colestipol, or colesevelam adsorb and reduce bile acid absorption and may reduce the absorption, systemic exposure, and efficacy of OCALIVA. If taking a bile acid binding resin, take OCALIVA at least 4 hours before or 4 hours after taking the bile acid binding resin, or at as great an interval as possible [see Dosage and Administration (2.5)].

7.2 Warfarin

The International Normalized Ratio (INR) decreased following coadministration of warfarin and OCALIVA [see Clinical Pharmacology (12.3)]. Monitor INR and adjust the dosage of warfarin, as needed, to maintain the target INR range when co-administering OCALIVA and warfarin.

7.3 CYP1A2 Substrates with Narrow Therapeutic Index

Obeticholic acid may increase the exposure to concomitant drugs that are CYP1A2 substrates [see Clinical Pharmacology (12.3)]. Therapeutic monitoring of CYP1A2 substrates with a narrow therapeutic index (e.g., theophylline and tizanidine) is recommended when co-administered with OCALIVA.

7.4 Inhibitors of Bile Salt Efflux Pump

Avoid concomitant use of inhibitors of the bile salt efflux pump (BSEP) such as cyclosporine [see Clinical Pharmacology (12.3)]. Concomitant medications that inhibit canalicular membrane bile acid transporters such as the BSEP may exacerbate accumulation of conjugated bile salts including taurine conjugate of obeticholic acid in the liver and result in clinical symptoms. If concomitant use is deemed necessary, monitor serum transaminases and bilirubin.

8 USE IN SPECIFIC POPULATIONS

8.1 Pregnancy

Risk Summary

The limited available human data on the use of obeticholic acid during pregnancy are not sufficient to inform a drug-associated risk. In animal reproduction studies, no developmental abnormalities or fetal harm was observed when pregnant rats or rabbits were administered obeticholic acid during the period of organogenesis at exposures approximately 13-times and 6-times human exposures, respectively, at the maximum recommended human dose (MRHD) of 10 mg [see Data below].

The estimated background risks of major birth defects and miscarriage for the indicated population are unknown. In the U.S. general population, the estimated background risk of major birth defects and miscarriage in clinically recognized pregnancies is 2% to 4% and 15% to 20%, respectively.

Data

Animal Data

In an embryo-fetal development study in rats, obeticholic acid was administered orally during the period of organogenesis at doses of 5, 25, and 75 mg/kg/day. At 25 mg/kg/day (a dose that produced systemic exposures approximately 13-times those in humans at the MRHD of 10 mg), there was no maternal or developmental toxicity. At 75 mg/kg/day (approximately 40-times the human exposure at the MRHD), decreased fetal body weights and increased numbers of early or late resorptions and nonviable fetuses were observed. In maternal animals, mortality, fetal loss, decreased body weight and food consumption as well as decreased body weight gain were observed at 75 mg/kg/day. Thus, the developmental toxicity observed at this dose may be secondary to maternal toxicity. In rabbits, obeticholic acid was administered orally during the period of organogenesis at doses of 3, 9, and 20 mg/kg/day. Obeticholic acid administered at doses up to 20 mg/kg/day (approximately 6-times the human exposure at the MRHD) was not teratogenic and did not produce any evidence of fetal harm.

In a pre- and post-natal development study, administration of obeticholic acid in rats during organogenesis through lactation at doses of 5, 25, and 40 mg/kg/day did not produce effects on pregnancy, parturition, or postnatal development at any dose (the 40 mg/kg/day dose is approximately 21-times the human exposure at the MRHD).

Obeticholic acid exposure margins were calculated using systemic exposure (AUC) values of obeticholic acid plus obeticholic acid's active metabolite conjugates (tauro-obeticholic acid and glyco-obeticholic acid) in animals (at the indicated doses) and in humans at the MRHD of 10 mg.

8.2 Lactation

Risk Summary

There is no information on the presence of obeticholic acid in human milk, the effects on the breast-fed infant or the effects on milk production. The developmental and health benefits of breastfeeding should be considered along with the mother's clinical need for OCALIVA and any potential adverse effects on the breastfed infant from OCALIVA or from the underlying maternal condition.

8.4 Pediatric Use

The safety and effectiveness of OCALIVA in pediatric patients have not been established.

8.5 Geriatric Use

Of the 201 patients in clinical trials of OCALIVA who received the recommended dosage (5 mg or 10 mg once daily), 41 (20%) were 65 years of age and older, while 9 (4%) were 75 years of age and older. No overall differences in safety or effectiveness were observed between these patients and patients less than 65 years of age, but greater sensitivity of some older individuals cannot be ruled out.

8.6 Hepatic Impairment

Hepatic decompensation and failure, sometimes fatal or resulting in liver transplant, have been reported with OCALIVA treatment in PBC patients with cirrhosis, either compensated or decompensated [see Warnings and Precautions (5.1)]. OCALIVA is contraindicated in patients with decompensated cirrhosis (e.g., Child-Pugh Class B or C), in those with a prior decompensation event, or with compensated cirrhosis who have evidence of portal hypertension (e.g., ascites, gastroesophageal varices, persistent thrombocytopenia) [see Contraindications (4)].

In PBC clinical trials, a dose-response relationship was observed for the occurrence of hepatic adverse reactions with OCALIVA [see Warnings and Precautions (5.1)].

Plasma exposure to obeticholic acid and its active conjugates, increases significantly in patients with moderate to severe hepatic impairment [see Clinical Pharmacology (12.3)].

Routinely monitor patients for progression of PBC with laboratory and clinical assessments. Closely monitor patients with compensated cirrhosis, concomitant hepatic disease, and/or severe intercurrent illness for new evidence of portal hypertension (e.g., ascites, gastroesophageal varices, persistent thrombocytopenia) or increases above the upper limit of normal in total bilirubin, direct bilirubin, or prothrombin time to determine whether drug discontinuation is needed. Permanently discontinue OCALIVA in patients who develop laboratory or clinical evidence of hepatic decompensation, have compensated cirrhosis and develop evidence of portal hypertension, or experience clinically significant hepatic adverse reactions while on treatment. Interrupt treatment during severe intercurrent illness [see Dosage and Administration (2.3), Warnings and Precautions (5.1)].

10 OVERDOSAGE

In the clinical trials, PBC patients who received OCALIVA 25 mg once daily (2.5-times the highest recommended dosage) or 50 mg once daily (5-times the highest recommended dosage) experienced a dose-dependent increase in the incidence of hepatic adverse reactions, including elevations in liver biochemical tests, ascites, jaundice, portal hypertension, and primary biliary cholangitis flares.

Serious hepatic adverse reactions have been reported postmarketing in PBC patients with decompensated cirrhosis when OCALIVA was dosed more frequently than the recommended dosage; these adverse reactions were also reported in some patients who received the recommended dosage [see Contraindications (4), Warnings and Precautions (5.1)].

In the case of overdosage, patients should be carefully observed, and supportive care administered, as appropriate.

11 DESCRIPTION

OCALIVA is a farnesoid X receptor (FXR) agonist. Chemically, obeticholic acid is 3α,7α-dihydroxy-6α-ethyl-5β-cholan-24-oic acid. It is a white to off-white powder. It is soluble in methanol, acetone and ethyl acetate. Its solubility in water is pH dependent. It is slightly soluble at low pH and very soluble at high pH. Its chemical formula is C26H44O4, the molecular weight is 420.63 g/mol, and the chemical structure is:

OCALIVA tablets are supplied in 5 mg and 10 mg strengths for oral administration. Each tablet contains obeticholic acid as the active ingredient and the following inactive ingredients: microcrystalline cellulose, sodium starch glycolate, and magnesium stearate. The film coating is Opadry II (Yellow) containing polyvinyl alcohol-part hydrolyzed, titanium dioxide, macrogol (polyethylene glycol 3350), talc, and iron oxide yellow.

12 CLINICAL PHARMACOLOGY

12.1 Mechanism of Action

Obeticholic acid is an agonist for FXR, a nuclear receptor expressed in the liver and intestine. FXR is a key regulator of bile acid, inflammatory, fibrotic, and metabolic pathways. FXR activation decreases the intracellular hepatocyte concentrations of bile acids by suppressing de novo synthesis from cholesterol as well as by increased transport of bile acids out of the hepatocytes. These mechanisms limit the overall size of the circulating bile acid pool while promoting choleresis, thus reducing hepatic exposure to bile acids.

12.2 Pharmacodynamics

Dose Titration

In Trial 1, ALP reduction was observed to plateau at approximately 3 months in most patients treated with OCALIVA 5 mg once daily. Increasing the dosage of OCALIVA to 10 mg once daily based on tolerability and response provided additional reduction in ALP in the majority of patients [see Dosage and Administration (2.2), Clinical Studies (14)].

Pharmacodynamic Markers

In Trial 1, administration of OCALIVA 10 mg once daily was associated with a 173% increase in concentrations of FGF-19, an FXR-inducible enterokine involved in bile acid homeostasis, from baseline to Month 12. Concentrations of cholic acid and chenodeoxycholic acid were reduced 2.7 micromolar and 1.4 micromolar, respectively, from baseline to Month 12. The clinical relevance of these findings is unknown.

Cardiac Electrophysiology

At a dose of 10-times the maximum recommended dose, OCALIVA does not prolong the QT interval to any clinically relevant extent.

12.3 Pharmacokinetics

Absorption

Following multiple oral doses of OCALIVA 10 mg once daily, peak plasma concentrations (Cmax) of obeticholic acid occurred at a median time (Tmax) of approximately 1.5 hours. The median Tmax for both the glyco- and tauro-conjugates of obeticholic acid was 10 hours. Coadministration with food did not alter the extent of absorption of obeticholic acid [see Dosage and Administration (2.5)].

Following multiple-dose administration of OCALIVA 5, 10, and 25 mg once daily (2.5-times the highest recommend dosage) for 14 days, systemic exposures of obeticholic acid increased dose proportionally. Exposures to glyco-obeticholic acid and tauro-obeticholic acid, and total obeticholic acid (the sum of obeticholic acid and its two active conjugates) increased more than proportionally with dose. The steady-state systemic exposure (AUC0-24h) achieved on Day 14 of total obeticholic acid was 4.2-, 6.6-, and 7.8- fold the systemic exposure (AUC0-24h) achieved on Day 1 after 5, 10, and 25 mg once daily dosing, respectively.

Distribution

Human plasma protein binding of obeticholic acid and its conjugates is greater than 99%. The volume of distribution of obeticholic acid is 618 L. The volumes of distribution of glyco- and tauro-obeticholic acid have not been determined.

Elimination

Metabolism

Obeticholic acid is conjugated with glycine or taurine in the liver and secreted into bile. These glycine and taurine conjugates of obeticholic acid are absorbed in the small intestine leading to enterohepatic recirculation. The conjugates can be deconjugated in the ileum and colon by intestinal microbiota, leading to the conversion to obeticholic acid that can be reabsorbed or excreted in feces, the principal route of elimination.

After daily administration of obeticholic acid, there was accumulation of the glycine and taurine conjugates of obeticholic acid, which have in vitro pharmacological activities similar to the parent drug, obeticholic acid. The metabolite-to-parent ratios of the glycine and taurine conjugates of obeticholic acid were 13.8 and 12.3 respectively, after daily administration. An additional third obeticholic acid metabolite, 3-glucuronide, was formed but was considered to have minimal pharmacologic activity.

Excretion

After administration of radiolabeled obeticholic acid, about 87% of the dose was excreted in feces through biliary secretion. Less than 3% of the dose was excreted in the urine with no detection of obeticholic acid.

Specific Populations

Body weight, Age, Sex Race/Ethnicity: Based on population pharmacokinetic analysis, body weight was a significant predictor of obeticholic acid pharmacokinetics with lower obeticholic acid exposure expected with higher body weight. The body weight effect is not expected to cause a meaningful impact on efficacy. The pharmacokinetics of obeticholic acid would not be expected to be altered based on age, sex, or race/ethnicity.

Renal Impairment: In a single-dose pharmacokinetic study using 25 mg of obeticholic acid (2.5-times the highest recommended dosage), mean AUC of total obeticholic acid was increased by approximately 1.4- to 1.6-fold in subjects with mild (eGFR 60 to 89 mL/min/1.73 m^2 using the modification of diet in renal disease [MDRD] equation), moderate (eGFR 30 to 59 mL/min/1.73 m^2 by MDRD), and severe (eGFR 15 to 29 mL/min/1.73 m^2 by MDRD) renal impairment compared to subjects with normal renal function. This increase is not considered to be clinically meaningful.

Hepatic Impairment: Obeticholic acid is metabolized in the liver. In subjects with mild, moderate, and severe hepatic impairment (Child-Pugh Class A, B, and C, respectively), the mean AUC of total obeticholic acid increased 1.1-, 4- and 17-fold, respectively, compared to subjects with normal hepatic function following single-dose administration of 10 mg OCALIVA [see Contraindications (4), Warnings and Precautions (5.1), Use in Specific Populations (8.6)].

Drug Interaction Studies

Effect of Obeticholic Acid on Other Drugs

Based on in vitro studies, obeticholic acid can inhibit CYP3A4. However, an in vivo study indicated no inhibition of CYP3A4 by obeticholic acid at the recommended dose of OCALIVA. Obeticholic acid is not expected to inhibit CYPs 2B6, 2C8, 2C9, 2C19, and 2D6, or induce CYPs 1A2, 2B6, 2C8, 2C9, 2C19, and 3A4 at the recommended dose of OCALIVA. Down-regulation of mRNA was observed in a concentration-dependent fashion for CYP1A2 and CYP3A4 by obeticholic acid and its glycine and taurine conjugates.

In vitro studies suggest that there is potential for obeticholic acid and its glycine and taurine conjugates to inhibit OATP1B1 and OATP1B3 (the clinical significance of which is unknown), but not P-gp, BCRP, OAT1, OAT3, OCT2, and MATE transporters, at the recommended dose of OCALIVA.

In vitro studies showed that obeticholic acid and its glycine and taurine conjugates inhibit BSEP in a dose dependent manner. However, an in vivo drug interaction due to inhibition of BSEP in patients using the recommended dosage regimen appears unlikely.

Induction of BSEP can occur by FXR activation by obeticholic acid and its conjugates, which are FXR agonists.

Warfarin: Concomitant administration of 25 mg warfarin as a single dose with OCALIVA 10 mg once daily resulted in 13% increase in systemic exposure to S-warfarin and 11% decrease in maximum INR [see Drug Interactions (7.2)].

Caffeine (CYP1A2 substrate): Concomitant administration of 200 mg caffeine as a single dose with OCALIVA 10 mg once daily resulted in a 42% increase in plasma AUC and 6% increase in Cmax of caffeine [see Drug Interactions (7.3)].

Omeprazole (CYP2C19 substrate): Concomitant administration of 20 mg omeprazole as a single dose with OCALIVA 10 mg once daily resulted in a 32% increase in AUC and a 33% increase in Cmax of omeprazole. The clinical significance is unknown.

No clinically relevant interactions were seen when the following drugs were administered as single doses concomitantly with OCALIVA 10 mg once daily:

Midazolam 2 mg (CYP3A4 substrate): 2% increase in AUC and Cmax of midazolam.

Dextromethorphan 30 mg (CYP2D6 substrate): 11% decrease in AUC and 12% decrease in Cmax of dextromethorphan.

Digoxin 0.25 mg (P-gp substrate): 1% increase in AUC and 3% decrease in Cmax of digoxin.

Rosuvastatin 20 mg (BCRP, OATP1B1, OATP1B3 substrate): 22% increase in AUC and a 27% increase in Cmax of rosuvastatin.

Effect of Other Drugs on Obeticholic Acid

In vitro data suggest that obeticholic acid is not metabolized to any significant extent by CYP450 enzymes.

Proton Pump Inhibitors (omeprazole): Concomitant administration of 20 mg omeprazole once daily with OCALIVA 10 mg once daily resulted in a less than 1.2-fold increase in obeticholic acid plasma exposure. This increase is not expected to be clinically meaningful. Concomitant administration of 40 mg omeprazole once daily with OCALIVA 10 mg once daily was not studied.

BSEP inhibitors: In vitro data indicate that tauro-obeticholic acid is a substrate of BSEP [see Drug Interactions (7.4)].

13 NONCLINICAL TOXICOLOGY

13.1 Carcinogenesis, Mutagenesis, Impairment of Fertility

Carcinogenic potential of obeticholic acid was assessed in carcinogenicity studies of up to 2 years in duration in mice and rats. In mice, there were no drug-related neoplastic findings at doses up to 25 mg/kg/day obeticholic acid, a dose that produced systemic exposures approximately 12-times those in humans at the MRHD of 10 mg. In rats, obeticholic acid was administered at doses of 2, 7, and 20 mg/kg/day. At 20 mg/kg/day (approximately 12-times the human exposure at the MRHD), obeticholic acid caused an increase in the incidence of benign granulosa cell tumors in the ovaries and benign granular cell tumors in the cervix and vagina of female rats. There were no drug-related neoplastic findings in male rats.

Obeticholic acid was not genotoxic in the Ames test, a human peripheral blood lymphocyte chromosomal aberration test, and a mouse micronucleus test. The glycine conjugate of obeticholic acid was also not genotoxic in an Ames test and human peripheral blood lymphocyte chromosome aberration test. The taurine conjugate of obeticholic acid was not genotoxic in an Ames test, and was negative in a human peripheral blood lymphocyte chromosomal aberration test in the presence of metabolic activation; the findings of the chromosomal aberration assay in the absence of metabolic activation were inconclusive.

Obeticholic acid, administered at oral doses of 5, 25, and 50 mg/kg/day to male rats for 28 days before mating and throughout the mating period, and to female rats from 14 days before mating through mating and until gestation day 7, did not alter male or female fertility or early embryonic development at any dose (the 50 mg/kg/day dose is approximately 13-times the human exposure at the MRHD).

14 CLINICAL STUDIES

The recommended starting dosage of OCALIVA is 5 mg orally once daily for 3 months with titration to 10 mg once daily based upon tolerability and response [see Dosage and Administration (2.2)]. Initiation of therapy with a starting dosage OCALIVA 10 mg once daily is not recommended due to an increased risk of pruritus [see Adverse Reactions (6.1)].

Trial 1 was a randomized, double-blind, placebo-controlled, 12-month clinical trial which evaluated the safety and efficacy of OCALIVA in 216 patients with PBC who were taking UDCA for at least 12 months (on a stable dosage for at least 3 months), or who were unable to tolerate UDCA and did not receive UDCA for at least 3 months. Patients were included in the trial if the ALP was 1.67-times upper limit of normal (ULN) or greater and/or if total bilirubin was greater than 1-times ULN but less than 2-times ULN. Patients were excluded from the trial if they had other liver disease, presence of clinically significant hepatic decompensation events (i.e., portal hypertension and its complications, cirrhosis with complications, or hepato-renal syndrome), severe pruritus, or Model for End Stage Liver Disease (MELD) score of 15 or greater.

Patients were randomized (1:1:1) to receive either OCALIVA 10 mg once daily for the entire 12 months of the trial, (n=73); OCALIVA titration (5 mg once daily for the initial 6 months, with the option to increase to 10 mg once daily for the last 6 months if the patient was tolerating OCALIVA but had ALP 1.67-times ULN or greater, and/or total bilirubin greater than ULN, or less than 15% ALP reduction) (n=70); or placebo (n=73). OCALIVA or placebo was administered in combination with UDCA in 93% of patients during the trial and as monotherapy in 7% of patients who were unable to tolerate UDCA.

The primary endpoint was a responder analysis at Month 12, where response was defined as a composite of three criteria: ALP less than 1.67-times the ULN, total bilirubin less than or equal to ULN, and an ALP decrease of at least 15%. The ULN for ALP was defined as 118 U/L for females and 124 U/L for males. The ULN for total bilirubin was defined as 1.1 mg/dL for females and 1.5 mg/dL for males.

The study population was 91% female and 94% white. The mean age was 56 years (range 29 to 86 years). The mean baseline ALP concentration was 323.2 U/L, corresponding to 2.74-times ULN. Approximately 29% of the patients had ALP concentration levels greater than 3-times the ULN. The mean baseline total bilirubin concentration was 0.65 mg/dL and was less than or equal to the ULN in 92% of the enrolled patients. Distribution of patients by Rotterdam disease stage criteria at baseline is shown in Table 2. Cirrhosis was present at baseline in 4 patients (5%) in the OCALIVA 10 mg arm, 7 patients (10%) in the OCALIVA titration arm, and 9 patients (12%) in the placebo arm.

Table 2: Rotterdam Disease Stage Criteria at Baseline in Trial 1 by Treatment Arm with or without UDCA [In the trial, there were 16 patients (7%) who were intolerant and did not receive concomitant UDCA: 6 patients (8%) in the OCALIVA 10 mg arm, 5 patients (7%) in the OCALIVA titration arm, and 5 patients (7%) in the placebo arm.]
Disease Stage [Early: normal total bilirubin and normal albumin (values less than or equal to ULN and greater than or equal to the lower limit of normal (LLN), respectively), Moderately advanced: abnormal total bilirubin or abnormal albumin, Advanced: abnormal total bilirubin and abnormal albumin. Total bilirubin ULN: 1.1 mg/dL (females) and 1.5 mg/dL (males). Albumin LLN: 35 g/L (females and males).] | OCALIVA 10 mg (N=73) | OCALIVA Titration (N=70) | Placebo (N=73)
Early, n (%) | 66 (90) | 64 (91) | 65 (89)
Moderately Advanced, n (%) | 7 (10) | 6 (9) | 8 (11)
Advanced, n (%) | 0 (0) | 0 (0) | 0 (0)
Percentages are based on non-missing values for each time point.

Table 3 shows the percentage of patients by treatment arm in Trial 1 who achieved a response to the primary composite endpoint at Month 12, and to the individual components of the primary endpoint (i.e., ALP less than 1.67-times the ULN, total bilirubin less than or equal to ULN, and an ALP decrease of at least 15%). A total of 33 patients in the OCALIVA titration arm, who did not achieve a response at 6 months and tolerated OCALIVA, had their dosage increased from 5 mg once daily to 10 mg once daily. Of these 33 patients, 13 (39%) achieved the primary composite endpoint at 12 months.

Table 3: Percentage of Adult Patients with PBC Achieving the Primary Composite Endpoint at Month 12 in Trial 1 by Treatment Arm with or without UDCA [In the trial, there were 16 patients (7%) who were intolerant and did not receive concomitant UDCA: 6 patients (8%) in the OCALIVA 10 mg arm, 5 patients (7%) in the OCALIVA titration arm, and 5 patients (7%) in the placebo arm.]
 | OCALIVA 10 mg (N=73) | OCALIVA Titration [Patients randomized to OCALIVA titration received OCALIVA 5 mg for the initial 6-month period. At Month 6, patients who were tolerating OCALIVA, but had an ALP 1.67-times ULN or greater, and/or total bilirubin greater than ULN, or less than 15% ALP reduction were eligible for titration from 5 mg once daily to 10 mg once daily for the final 6 months of the trial.] (N=70) | Placebo (N=73)
Primary Composite Endpoint [Percentage of patients achieving a response, defined as an ALP less than 1.67-times the ULN, total bilirubin less than or equal to the ULN, and an ALP decrease of at least 15%. Missing values were considered a non-response. The exact test was used to calculate the 95% CIs.]
Responder rate, (%) [p<0.0001 for OCALIVA titration and OCALIVA 10 mg arms versus placebo. P-values are obtained using the Cochran–Mantel–Haenszel General Association test stratified by intolerance to UDCA and pretreatment ALP greater than 3-times ULN and/or AST greater than 2-times ULN and/or total bilirubin greater than ULN.] | 48 | 46 | 10
[95% CI] | [36, 60] | [34, 58] | [4, 19]
Components of Primary Endpoint [Response rates were calculated based on the observed case analysis (i.e., [n=observed responder]/[N=ITT population]); percentage of patients with Month 12 values are 86%, 91%, and 96% for the OCALIVA 10 mg, OCALIVA titration and placebo arms, respectively.]
ALP less than 1.67-times ULN, n (%) | 40 (55) | 33 (47) | 12 (16)
Decrease in ALP of at least 15%, n (%) | 57 (78) | 54 (77) | 21 (29)
Total bilirubin less than or equal to ULN [The mean baseline total bilirubin value was 0.65 mg/dL, and was less than or equal to the ULN in 92% of the enrolled patients.] , n (%) | 60 (82) | 62 (89) | 57 (78)

Mean Reduction in ALP

Figure 1 shows the mean reductions in ALP in OCALIVA-treated patients compared to placebo. Reductions were observed as early as Week 2, plateaued by Month 3 and were maintained through Month 12 for patients who were maintained on the same dosage throughout 12 months. Although Trial 1 studied titration at 6 months, these data are supportive of titration of OCALIVA after 3 months [see Dosage and Administration (2.2)]. For patients in the OCALIVA titration arm whose OCALIVA dosage was increased from 5 mg once daily to 10 mg once daily, additional reductions in ALP were observed at Month 12 in the majority of patients [see Clinical Pharmacology (12.2)].

Figure 1: Mean ALP over 12 Months in Trial 1 by Treatment Arm with or without UDCAa

a | In the trial there were 16 patients (7%) who were intolerant and did not receive concomitant UDCA: 6 patients (8%) in the OCALIVA 10 mg arm, 5 patients (7%) in the OCALIVA titration arm, and 5 patients (7%) in the placebo arm.
b | Patients randomized to OCALIVA titration received OCALIVA 5 mg once daily for the initial 6-month period. At Month 6, patients who were tolerating OCALIVA, but had an ALP 1.67-times ULN or greater, and/or total bilirubin greater than ULN, or less than 15% ALP reduction were eligible for titration from 5 mg once daily to 10 mg once daily for the final 6 months of the trial.

Mean Reduction in GGT

The mean (95% CI) reduction in gamma-glutamyl transferase (GGT) was 178 (137, 219) U/L in the OCALIVA 10 mg arm, 138 (102, 174) U/L in the OCALIVA titration arm, and 8 (-32, 48) U/L in the placebo arm.

OCALIVA Monotherapy

Fifty-one PBC patients with baseline ALP 1.67-times ULN or greater and/or total bilirubin greater than ULN were evaluated for a biochemical response to OCALIVA as monotherapy (24 patients received OCALIVA 10 mg once daily and 27 patients received placebo) in a pooled analysis of data from Trial 1 and from a randomized, double-blind, placebo-controlled, 3-month clinical trial. At Month 3, 9 (38%) OCALIVA-treated patients achieved a response to the composite endpoint, compared to 1 (4%) placebo-treated patient. The mean (95% CI) reduction in ALP in OCALIVA-treated patients was 246 (165, 327) U/L compared to an increase of 17 (-7, 42) U/L in the placebo-treated patients.

16 HOW SUPPLIED/STORAGE AND HANDLING

OCALIVA tablets are packaged in a 40 mL high density polyethylene bottle closed with a 33 mm polypropylene child resistant cap containing an induction seal. Each bottle contains 30 tablets.

5 mg Tablets

OCALIVA tablets are available as off-white to yellow, round tablets debossed with INT on one side and 5 on the other side. Each tablet contains 5 mg of obeticholic acid.

- NDC 69516-005-30 | 5 mg tablets in a bottle (30 count)

10 mg Tablets

OCALIVA tablets are available as off-white to yellow, triangular tablets debossed with INT on one side and 10 on the other side. Each tablet contains 10 mg of obeticholic acid.

- NDC 69516-010-30 | 10 mg tablets in a bottle (30 count)

Storage and Handling

Store at 20°C to 25°C (68°F to 77°F); excursions permitted to 15°C to 30°C (59°F to 86°F) [See USP Controlled Room Temperature].

17 PATIENT COUNSELING INFORMATION

Advise the patient to read the FDA-approved patient labeling (Medication Guide).

Hepatic Decompensation and Failure in PBC Patients with Cirrhosis

- Instruct patients and caregivers to immediately contact their healthcare provider if they experience:
  - Symptoms of disease progression or worsening liver function, such as ascites, jaundice, variceal bleeding, or hepatic encephalopathy.
  - Symptoms of complete biliary obstruction [see Contraindications (4), Warnings and Precautions (5.1)].
  - Severe or persistent non-specific signs and symptoms of impaired health:
    - nausea, vomiting, abdominal pain, diarrhea, weight loss, fever and chills, worsening or new fatigue, weakness, loss of appetite, or dehydration.
- Inform patients that they will need to undergo laboratory testing periodically while on OCALIVA treatment to assess liver function.

Severe Pruritus

- Advise patients to contact their healthcare provider if they experience new onset or worsening severe pruritus [see Warnings and Precautions (5.2)].

Reduction in HDL-C

- Advise patients that they may need to undergo laboratory testing to check for changes in lipid levels while on treatment with OCALIVA [see Warnings and Precautions (5.3)].

Administration

Advise patients to take:

- OCALIVA with or without food.
- OCALIVA at least 4 hours before or 4 hours after taking a bile acid binding resin, or at as great an interval as possible [see Drug Interactions (7.1)].

OCALIVA is a registered trademark of Intercept Pharmaceuticals, Inc.

Distributed by:

Intercept Pharmaceuticals, Inc.

305 Madison Avenue
Morristown, NJ 07960

MEDICATION GUIDE
OCALIVA® (o-CAL-eh-vah)
(obeticholic acid) tablets

What is the most important information I should know about OCALIVA?

- Before you start OCALIVA, and during your treatment with OCALIVA, your healthcare provider will do tests to check your liver. These tests will help your healthcare provider decide if it is safe for you to start taking OCALIVA and safe for you to continue taking OCALIVA.

OCALIVA can cause serious side effects including:
Worsening of liver problems or liver failure, in some cases leading to liver transplant or death, has happened in people with primary biliary cholangitis (PBC) with liver cirrhosis when taking OCALIVA.

- Tell your healthcare provider right away if you have any of the following symptoms of worsening liver problems during treatment with OCALIVA:

- swelling of your stomach-area from a build-up of fluid
- yellowing of your skin or the whites of your eyes
- black, tarry, or bloody stools
- coughing up or vomiting blood, or your vomit looks like "coffee grounds"

- mental changes such as confusion, sleepier than usual or harder to wake up, slurred speech, mood swings, or changes in personality

- Tell your healthcare provider right away if you have any of the following symptoms during treatment with OCALIVA and they are severe or do not go away:

- stomach-area pain
- nausea, vomiting, or diarrhea
- loss of appetite or weight loss
- new or worsening fatigue

- weakness
- fever and chills
- light-headedness
- less frequent urination

What is OCALIVA?
OCALIVA is a prescription medicine used to treat primary biliary cholangitis (PBC) in combination with ursodeoxycholic acid (UDCA) in adults who have not responded well enough to UDCA, or alone in adults who cannot tolerate UDCA.
It is not known if taking OCALIVA will improve your chance of survival or improve your symptoms of PBC.
It is not known if OCALIVA is safe and effective in children.

Do not take OCALIVA if you:

- have PBC with liver cirrhosis with symptoms such as fluid in the stomach-area or confusion (decompensated liver cirrhosis) or with abnormalities in certain tests that check your liver.
- have a complete blockage of the bile ducts in your liver or gallbladder.

Before taking OCALIVA, tell your healthcare provider about all of your medical conditions, including if you:

- are pregnant or plan to become pregnant. It is not known if OCALIVA will harm your unborn baby.
- are breastfeeding or plan to breastfeed. It is not known if OCALIVA passes into your breast milk. Talk with your healthcare provider about the best way to feed your baby if you take OCALIVA.

Tell your healthcare provider about all the medicines you take, including prescription and over-the-counter medicines, vitamins, and herbal supplements. OCALIVA can affect the way certain medicines work. Certain other medicines may affect the way OCALIVA works.

How should I take OCALIVA?

- Take OCALIVA exactly as your healthcare provider tells you to.
- Do not take more OCALIVA than your healthcare provider tells you to.
- Take OCALIVA with or without food.
- If you take a bile acid binding resin, take OCALIVA at least 4 hours before or 4 hours after you take your bile acid binding resin. If this is not possible, space the time between taking OCALIVA and your bile acid binding resin as far apart as possible.
- If you take too much OCALIVA, call your healthcare provider or get emergency medical help right away.

What are the possible side effects of OCALIVA?
OCALIVA can cause serious side effects, including:

- See "What is the most important information I should know about OCALIVA?"
- Severe itching (pruritus). Itching is a common side effect of OCALIVA and can sometimes become severe (intense itching or itching over much of your body). Severe itching can cause discomfort, problems sleeping, and problems doing daily activities and usually needs to be treated. Tell your healthcare provider if you get severe itching or if your itching gets worse.
- Lower HDL-C ("good" cholesterol). OCALIVA can lower high levels of HDL-C. Your healthcare provider will check your cholesterol levels during your treatment with OCALIVA.

The most common side effects of OCALIVA include:

- tiredness
- stomach pain and discomfort
- rash
- joint pain
- mouth and throat pain

- dizziness
- constipation
- swelling in your hands, ankles, or feet
- fast or irregular heartbeat

- fever
- changes in how your thyroid gland works
- dryness, irritation, redness, crusting or drainage of the skin (eczema)

These are not all the possible side effects of OCALIVA. Call your doctor for medical advice about side effects. You may report side effects to FDA at 1-800-FDA-1088.

How should I store OCALIVA?

- Store OCALIVA at room temperature between 68°F to 77°F (20°C to 25°C).

Keep OCALIVA and all medicines out of the reach of children.

General information about the safe and effective use of OCALIVA.
Medicines are sometimes prescribed for purposes other than those listed in a Medication Guide. Do not use OCALIVA for a condition for which it was not prescribed. Do not give OCALIVA to other people, even if they have the same symptoms that you have. It may harm them. You can ask your pharmacist or healthcare provider for information about OCALIVA that is written for health professionals.

What are the ingredients in OCALIVA?
Active ingredient: obeticholic acid
Inactive ingredients: microcrystalline cellulose, sodium starch glycolate, magnesium stearate
Film coating: Opadry II (Yellow) containing polyvinyl alcohol-part hydrolyzed, titanium dioxide, macrogol (polyethylene glycol 3350), talc, iron oxide yellow
Distributed by: Intercept Pharmaceuticals, Inc., Morristown, NJ 07960
OCALIVA is a registered trademark of Intercept Pharmaceuticals, Inc.
For more information, go to www.OCALIVA.com or call 1-844-782-4278.

This Medication Guide has been approved by the U.S. Food and Drug Administration.

Revised: April 2022

PRINCIPAL DISPLAY PANEL - 5 mg Tablet Bottle Label

NDC 69516-005-30
Rx only

OCALIVA®
(obeticholic acid) tablets

5 mg

30 tablets
Intercept

PRINCIPAL DISPLAY PANEL - 10 mg Tablet Bottle Label

NDC 69516-010-30
Rx only

OCALIVA®
(obeticholic acid) tablets

10 mg

30 tablets
Intercept